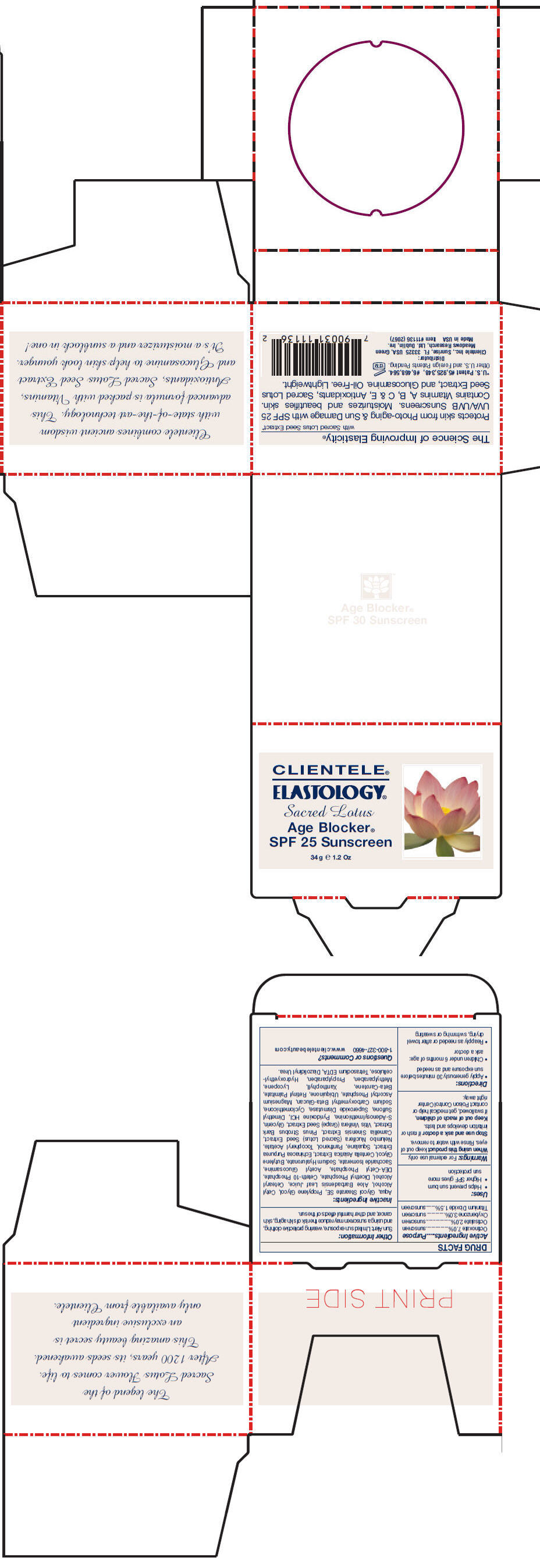 DRUG LABEL: Elastology Age Blocker
NDC: 64483-001 | Form: CREAM
Manufacturer: Clientele, Inc.
Category: otc | Type: HUMAN OTC DRUG LABEL
Date: 20110901

ACTIVE INGREDIENTS: Octinoxate 7 g/100 g; Octisalate 2 g/100 g; Titanium dioxide 1.5 g/100 g; Oxybenzone 3 g/100 g
INACTIVE INGREDIENTS: Glycerin 1 g/100 g; Alpha-Tocopherol 1 g/100 g; Panthenol 1 g/100 g; Water 54.47 g/100 g; Vitamin A 120000 [iU]/100 g; Cholecalciferol 12000 [iU]/100 g

ELASTOLOGY®
Sacred Lotus
Age Blocker®

ACTIVE INGREDIENT

Active Ingredients | Purpose
Octinoxate 7.0% | sunscreen
Octisalate 2.0% | sunscreen
Oxybenzone 3.0% | sunscreen
Titanium Dioxide 1.5% | sunscreen

Uses

- Helps prevent sun burn
- Higher SPF gives more sun protection

Warnings

For external use only.

When using this product keep out of eyes. Rinse with water to remove.

Stop use and ask a doctor if rash or irritation develops and lasts.

Keep out of reach of children, if swallowed, get medical help or contact Poison Control Center right away.

Directions

- Apply generously 30 minutes before sun exposure and as needed
- Children under 6 months of age: ask a doctor
- Reapply as needed or after towel drying, swimming or sweating

Other Information

Sun Alert: Limited sun exposure, wearing protective clothing, and using a sunscreen may reduce the risk of skin aging, skin cancer, and other harmful effects of the sun.

Inactive Ingredients

Aqua, Glycol Stearate SE, Propylene Glycol, Cetyl Alcohol, Aloe Barbadensis Leaf Juice, Cetearyl Alcohol, Dicethyl Phosphate, Ceteth-10 Phosphate, DEA-Cetyl Phosphate, Acetyl Glucosamine, Saccharide Isomerate, Sodium Hyaluronate, Butylene Glycol, Centella Asiatica Extract, Echinacea Purpurea Extract, Squalane, Panthenol, Tocopheryl Acetate, Nelumbo Nucifera (Sacred Lotus) Seed Extract, Camellia Sinensis Extract, Pinus Strobus Bark Extract, Vitis Vinifera (Grape) Seed Extract, Glycerin, S-Adenosylmethionine, Pyridoxine HCl, Dimethyl Sulfone, Superoxide Dismutase, Cyclomethicone, Sodium Carboxymethyl Beta-Glucan, Magnesium Ascorbyl Phosphate, Ubiquinone, Retinyl Palmitate, Beta-Carotene, Xanthophyll, Lycopene, Methylparaben, Propylparaben, Hydroxyethylcellulose, Tetrasodium EDTA, Diazolidinyl Urea.

Questions or Comments?

1-800-327-4660

www.clientelebeauty.com

Distributor:
Clientele Inc., Sunrise, FL 33325 USA

PRINCIPAL DISPLAY PANEL - 34 g Jar Carton

CLIENTELE®
ELASTOLOGY®

Sacred Lotus

Age Blocker®
SPF 25 Sunscreen

34 g e 1.2 Oz